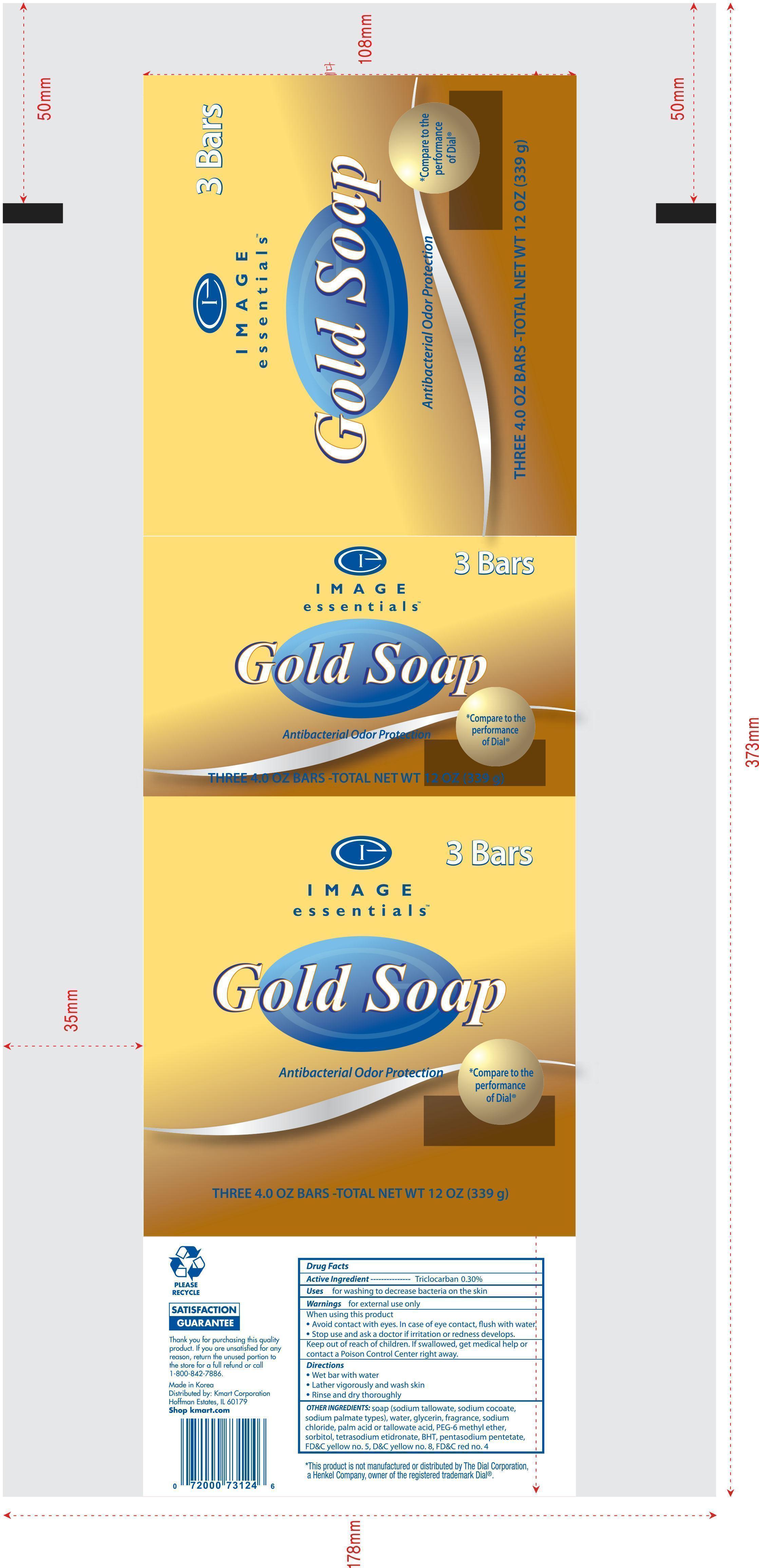 DRUG LABEL: Image Essentials Gold
NDC: 49738-731 | Form: SOAP
Manufacturer: Kmart Corporation
Category: otc | Type: HUMAN OTC DRUG LABEL
Date: 20140730

ACTIVE INGREDIENTS: TRICLOCARBAN 0.3 g/100 g
INACTIVE INGREDIENTS: SODIUM TALLOWATE, BEEF; SODIUM COCOATE; SODIUM PALMATE; WATER; GLYCERIN; SODIUM CHLORIDE; PALM ACID; PEG-6 METHYL ETHER; SORBITOL; ETIDRONATE TETRASODIUM; PENTASODIUM PENTETATE; FD&C YELLOW NO. 5; FD&C RED NO. 4

Active Ingredient-----------------------------------------------------Triclocarban 0.30%

PURPOSE

For washing to decrease bacteria on the skin.

Warnings For external use only

when using this product

- Avoid contact with eyes. In case of eye contact, flush with water.
- Stop usee and ask a doctor if irritation and redness develops.

KEEP OUT OF REACH OF CHILDREN

Keep out of reach of childern. if swallowed, get medical help or contact a Poison Control Center right away.

Directions

- Wet bar with water
- Lather vigorously and watsh skin
- rinse and dry thoroughly

INACTIVE INGREDIENT

Other ingredients: soap (sodium tallowate, sodium cocoate, sodium palmate types), water, glycerin, fragrance, sodium chloride, palm acid or tallowate acid, PEG-6 methyl ether, sorbitol, tetrasodium etidronate, BHT, pentasodium pentetate, FD&C yellow no. 5, D&C yellow no. 8, FD&C red no. 4

DOSAGE AND ADMINISTRATION

Distributed by

K Mart Corporation

Hoffman Estate, IL 60179

Shop kmart.com